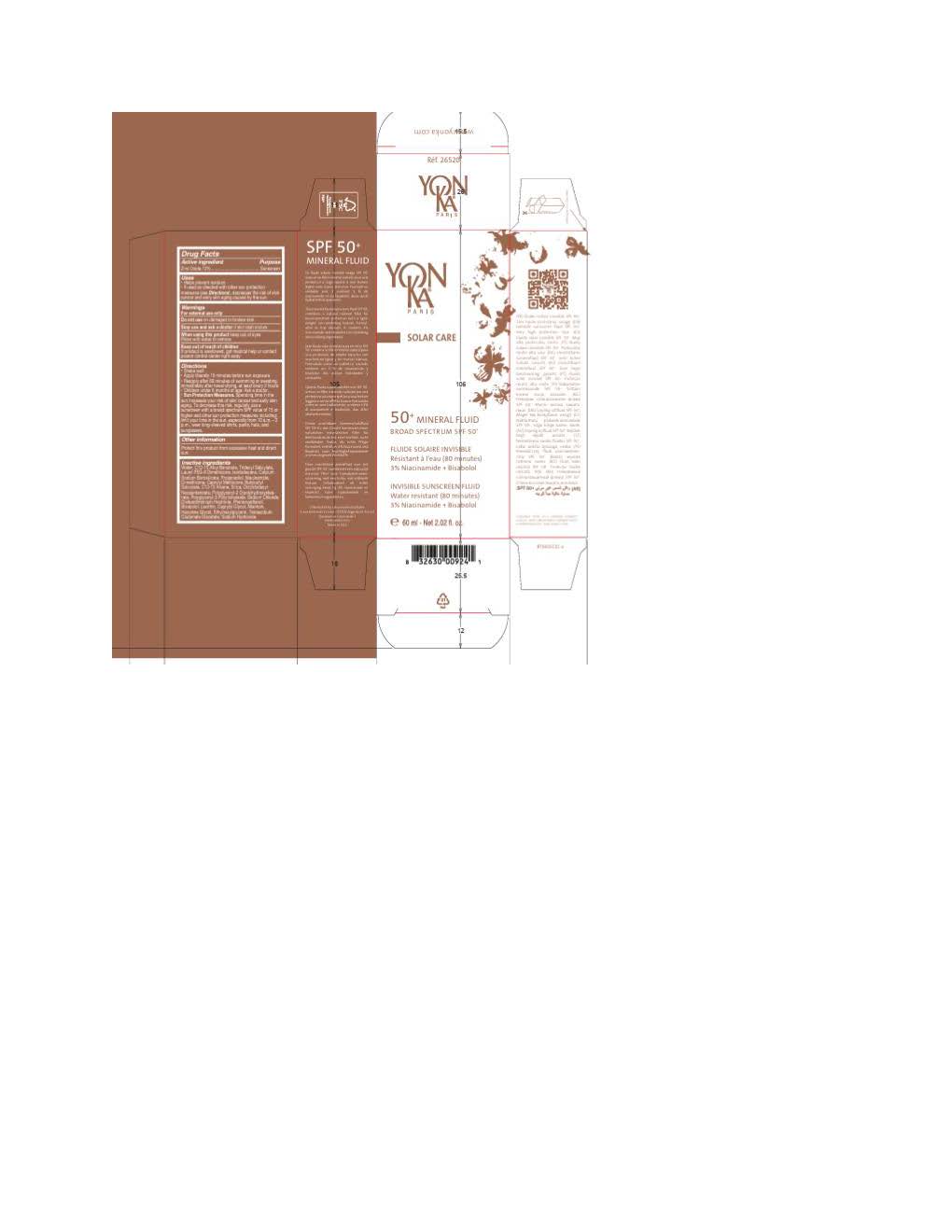 DRUG LABEL: Yon-Ka 50 Mineral Fluid
NDC: 51191-2667 | Form: LOTION
Manufacturer: Laboratoire MULTALER Yon-Ka
Category: otc | Type: HUMAN OTC DRUG LABEL
Date: 20260105

ACTIVE INGREDIENTS: ZINC OXIDE 132 mg/1 mL
INACTIVE INGREDIENTS: SODIUM HYDROXIDE; POLYGLYCERYL-2 DIPOLYHYDROXYSTEARATE; OCTYLDODECYL NEOPENTANOATE; LECITHIN, SOYBEAN; CAPRYLYL GLYCOL; DIMETHICONE 200; ALKYL (C12-15) BENZOATE; .ALPHA.-BISABOLOL, (+)-; LAURYL PEG-8 DIMETHICONE (300 CPS); BUTYLOCTYL SALICYLATE; ISODODECANE; WATER; NIACINAMIDE; ETHYLHEXYLGLYCERIN; HEXYLENE GLYCOL; PROPANEDIOL; TETRASODIUM GLUTAMATE DIACETATE; SODIUM CHLORIDE; PHENOXYETHANOL; ALLANTOIN; CAPRYLYL METHICONE; C13-15 ALKANE; DISTEARDIMONIUM HECTORITE; CALCIUM SODIUM BOROSILICATE; TRIDECYL SALICYLATE; SILICON DIOXIDE

Yon-Ka 50 Mineral Fluid